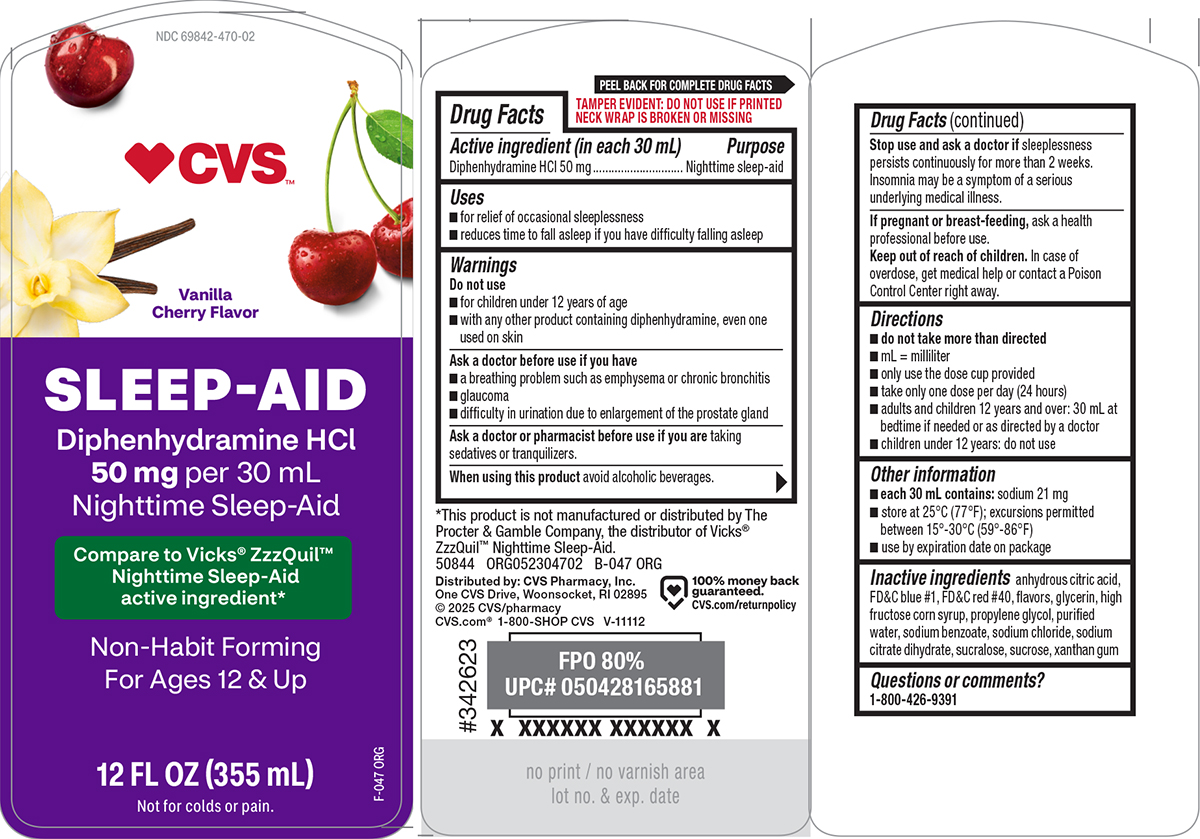 DRUG LABEL: Sleep-Aid
NDC: 69842-470 | Form: SOLUTION
Manufacturer: CVS PHARMACY
Category: otc | Type: HUMAN OTC DRUG LABEL
Date: 20250916

ACTIVE INGREDIENTS: DIPHENHYDRAMINE HYDROCHLORIDE 50 mg/30 mL
INACTIVE INGREDIENTS: ANHYDROUS CITRIC ACID; FD&C BLUE NO. 1; FD&C RED NO. 40; GLYCERIN; HIGH FRUCTOSE CORN SYRUP; PROPYLENE GLYCOL; WATER; SODIUM BENZOATE; SODIUM CHLORIDE; TRISODIUM CITRATE DIHYDRATE; SUCRALOSE; SUCROSE; XANTHAN GUM

CVS 44-047

Active ingredient (in each 30 mL)

Diphenhydramine HCl 50 mg

Purpose

Nighttime sleep-aid

Uses

- for relief of occasional sleeplessness
- reduces time to fall asleep if you have difficulty falling asleep

Warnings

Do not use

- for children under 12 years of age
- with any other product containing diphenhydramine, even one used on skin

Ask a doctor before use if you have

- glaucoma
- a breathing problem such as emphysema or chronic bronchitis
- difficulty in urination due to enlargement of the prostate gland

Ask a doctor or pharmacist before use if you are

taking sedatives or tranquilizers.

When using this product

avoid alcoholic beverages.

Stop use and ask a doctor if

sleeplessness persists continuously for more than 2 weeks. Insomnia may be a symptom of a serious underlying medical illness.

If pregnant or breast-feeding,

ask a health professional before use.

Keep out of reach of children.

In case of overdose, get medical help or contact a Poison Control Center right away.

Directions

- do not take more than directed
- mL = milliliter
- only use the dose cup provided
- take only one dose per day (24 hours)
- adults and children 12 years and over: 30 mL at bedtime if needed or as directed by a doctor
- children under 12 years: do not use

Other information

- each 30 mL contains: sodium 21 mg
- store at 25ºC (77ºF); excursions permitted between 15º-30ºC (59º-86ºF)
- use by expiration date on package

Inactive ingredients

anhydrous citric acid, FD&C blue #1, FD&C red #40, flavors, glycerin, high fructose corn syrup, propylene glycol, purified water, sodium benzoate, sodium chloride, sodium citrate dihydrate, sucralose, sucrose, xanthan gum

Questions or comments?

1-800-426-9391

Principal Display Panel

NDC 69842-470-02

♥CVS™

Vanilla
Cherry Flavor

SLEEP-AID
DIPHENHYDRAMINE HCl
50 mg per 30 mL
Nighttime Sleep-Aid

Compare to Vicks® ZzzQuil™
Nighttime Sleep-Aid
active ingredient*

Non-Habit Forming
For Ages 12 & Up

12 FL OZ (355 mL)
Not for colds or pain.

TAMPER EVIDENT: DO NOT USE IF PRINTED
NECK WRAP IS BROKEN OR MISSING

*This product is not manufactured or distributed by The
Procter & Gamble Company, the distributors of Vicks®
ZzzQuil™ Nighttime Sleep-Aid.

50844 ORG052304702

Distributed by: CVS Pharmacy, Inc.
One CVS Drive, Woonsocket, RI 02895
© 2025 CVS/pharmacy
CVS.com® 1-800-SHOP CVS V-11112

100% money back
guaranteed.
CVS.com/returnpolicy

CVS 44-047